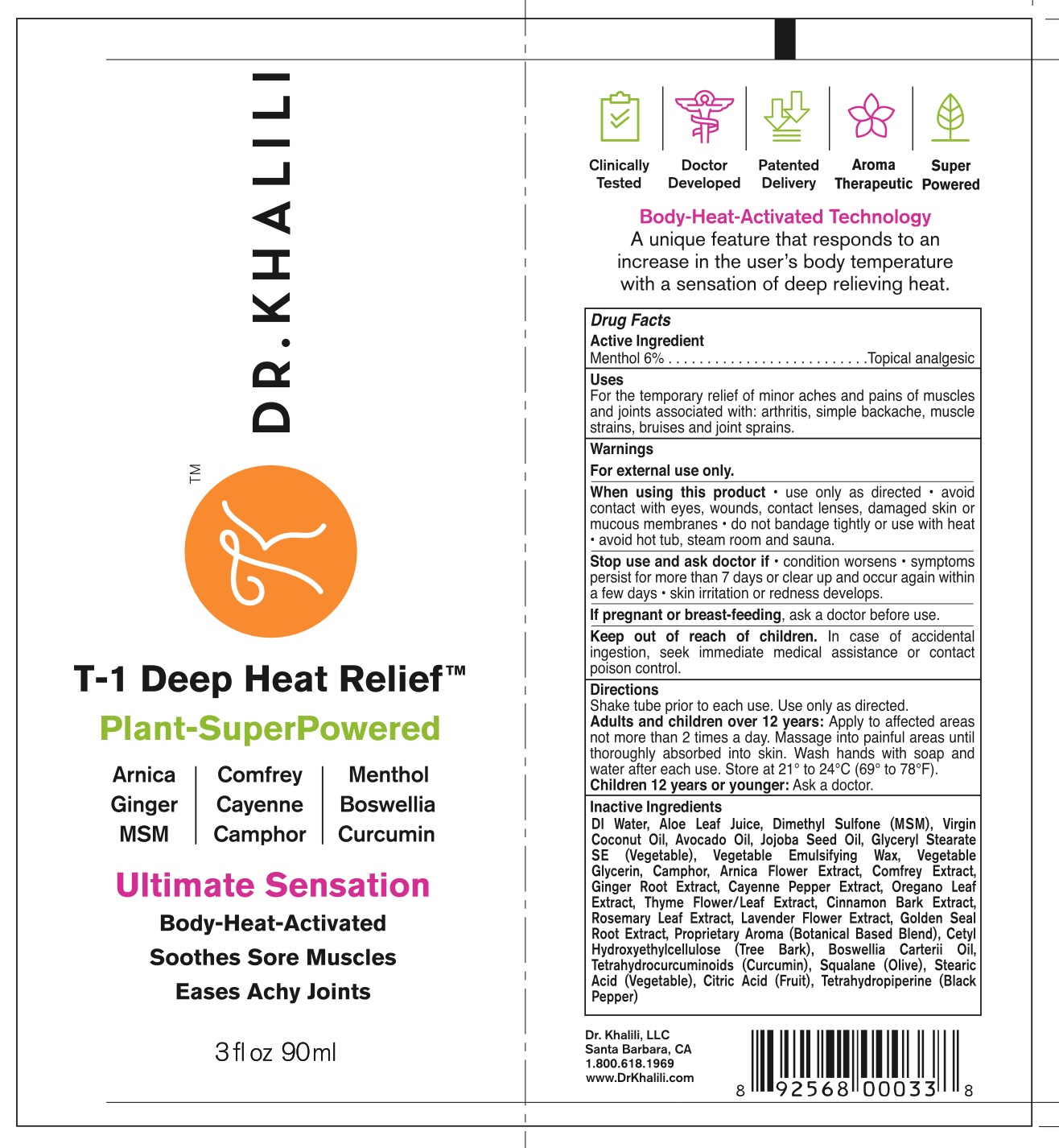 DRUG LABEL: Dr Kevin Khalili Pain Relief Cream
NDC: 85953-001 | Form: CREAM
Manufacturer: DR. KHALILI LLC
Category: otc | Type: HUMAN OTC DRUG LABEL
Date: 20250721

ACTIVE INGREDIENTS: MENTHOL 6 g/100 g
INACTIVE INGREDIENTS: LAVENDER OIL; GOLDENSEAL; COMFREY; CETYL HYDROXYETHYLCELLULOSE (350000 MW); STEARETH-20; CINNAMON OIL; CETEARYL ALCOHOL; PEG-150 STEARATE; GLYCERIN; ARNICA MONTANA FLOWER; GINGER; CURCUMIN; ALOE BARBADENSIS LEAF JUICE; AVOCADO OIL; JOJOBA OIL; GLYCERYL STEARATE; POLYSORBATE 60; CAMPHOR OIL; THYME; SQUALANE; STEARIC ACID; CITRIC ACID; TETRAHYDROPIPERINE; WATER; DIMETHYL SULFONE; OREGANO; BOSWELLIA CARTERII OIL; COCONUT OIL; CAPSICUM ANNUUM WHOLE; ROSEMARY OIL

Dr. Kevin Khalili Pain Relief Cream

ACTIVE INGREDIENT

Menthol 6%

PURPOSE

.Topical analgesic

USES

For the temporary relief of minor aches and pains of muscles and joints associated with: arthritis, simple backache, muscle strains, bruises and joint sprains

WARNINGS

For external use only.

When using this product

use only as directed • avoid contact with eyes, wounds, contact lenses, damaged skin or mucous membranes • do not bandage tightly or use with heat

• avoid hot tub, steam room and

Stop use and ask doctor if

condition worsens • symptoms persist for more than 7 days or clear up and occur again within a few days • skin irritation or redness develops.

If pregnant or breast-feeding

ask a doctor before use.

Keep out of reach of children

In case of accidental ingestion, seek immediate medical assistance or contact poison control.

DIRECTIONS

Shake tube prior to each use. Use only as directed.

Adults and children over 12 years: Apply to affected areas not more than 2 times a day. Massage into painful areas until thoroughly absorbed into skin. Wash hands with soap and Store a 21/102

water after each use. Store at 21° to 24°C (69° to 78°F).

Children 12 years or younger: Ask a doctor.

INACTIVE INGREDIENTS

DI Water, Aloe Leat Juice, Dimethyl Sulfone (MSM), Virgin Coconut Oil, Avocado Oil, Jojoba Seed Oil, Glyceryl Stearate

SE (Vegetable), Vegetable Emulsifying Vegetable Glycerin, Camphor, Arnica Flower Extract, Comfrey Extract, Ginger Root Extract, Cayenne Pepper Extract, Oregano Leaf Extract, Thyme Flower/Leaf Extract, Cinnamon Bark Extract, Rosemary Leaf Extract, Lavender Flower Extract, Golden Seal Root Extract, Proprietary Aroma (Botanical Based Blend), Cetyl Hydroxyethylcellulose (Tree Bark), Boswellia Carterii Oil, Tetrahydrocurcuminoids (Curcumin), Squalane (Olive), Stearic Acid (Vegetable), Citric Acid (Fruit), Tetrahydropiperine (Black Pepper)